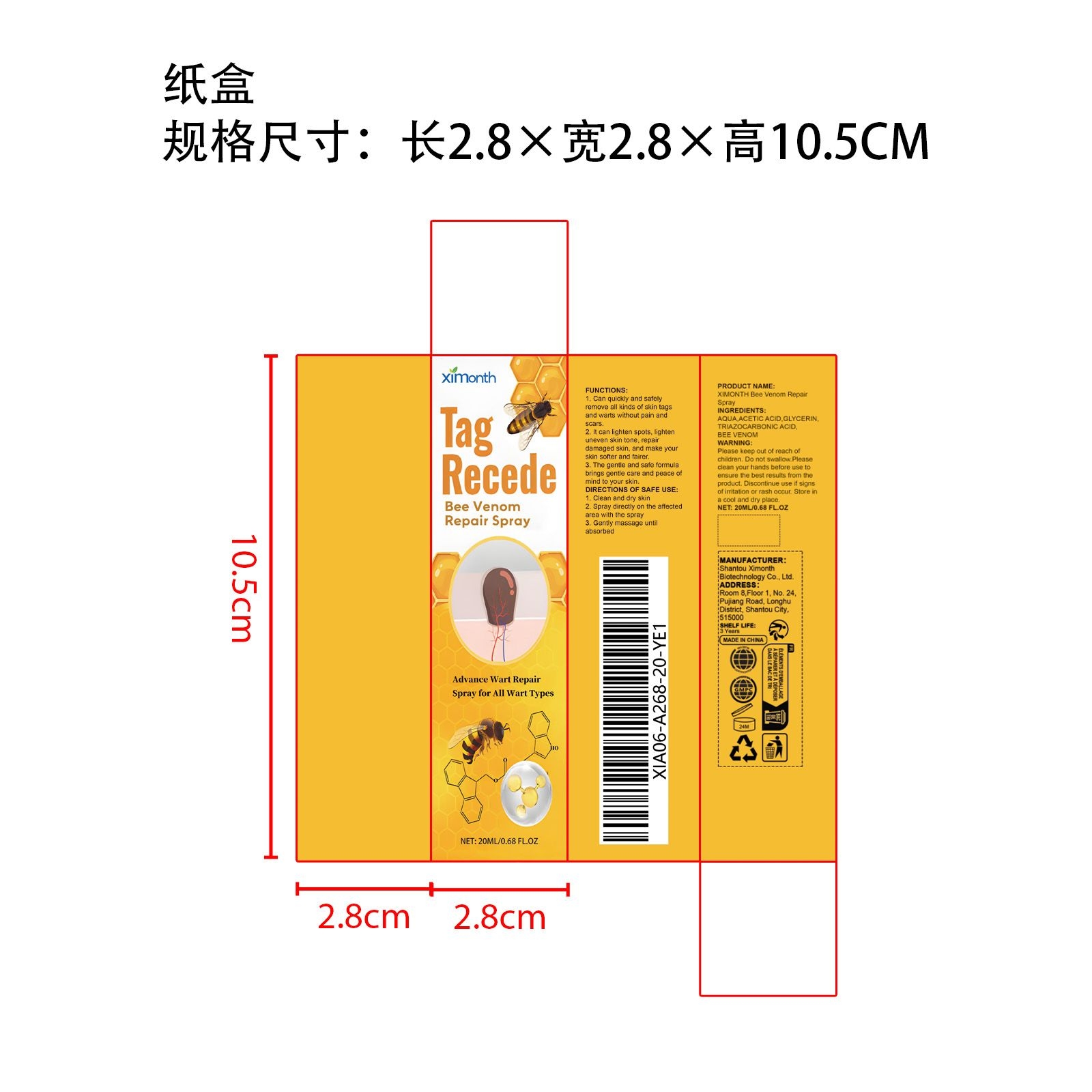 DRUG LABEL: XIMONTH Bee Venom Repair
NDC: 84989-006 | Form: LIQUID
Manufacturer: Shantou Ximonth Biotechnology Co., Ltd.
Category: otc | Type: HUMAN OTC DRUG LABEL
Date: 20251126

ACTIVE INGREDIENTS: APIS MELLIFERA VENOM 0.004 mg/20 mg
INACTIVE INGREDIENTS: AQUA 18.396 mg/20 mg; TRIAZOLAM 0.2 mg/20 mg; ACETIC ACID 1 mg/20 mg; GLYCERIN 0.4 mg/20 mg

ACTIVE INGREDIENT

APIS MELLIFERA VENOM

WHEN USING

1. Clean and dry skin

2. Spray directly on the affected area with the spray

3. Gently massage until absorbed

PURPOSE

1. Can quickly and safely remove all kinds of skin tags and warts without pain and scars.

2. It can lighten spots, lighten uneven skin tone, repair damaged skin, and make your skin softer and fairer.

3. The gentle and safe formula brings gentle care and peace of mind to your skin.

WARNINGS

Please keep out of reach of children. Do not swallow.Please clean your hands before use to ensure the best results from the product. Discontinue use if signs of irritation or rash occur. Store in a cool and dry place.

STOP USE

Discontinue use if signs of irritation or rash occur.

DO NOT USE

Discontinue use if signs of irritation or rash occur.

KEEP OUT OF REACH OF CHILDREN

Please keep out of reach of children. Do not swallow.

STORAGE AND HANDLING

Store in a cool and dry place.

INACTIVE INGREDIENT

AQUA、ACETIC ACID、GLYCERIN、TRIAZOCARBONIC ACID